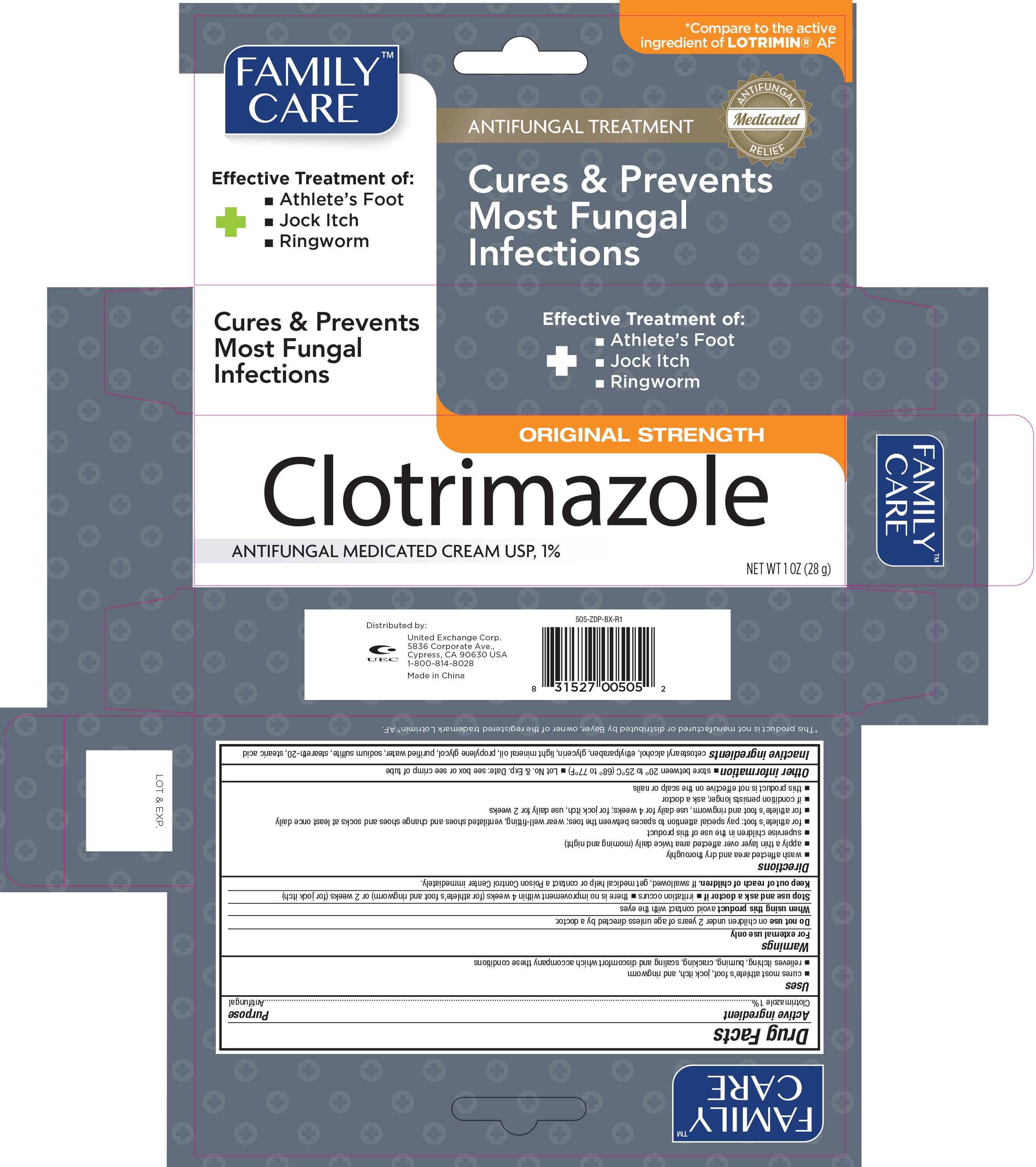 DRUG LABEL: Family Care Antifungal
NDC: 65923-052 | Form: CREAM
Manufacturer: United Exchange Corp.
Category: otc | Type: HUMAN OTC DRUG LABEL
Date: 20251030

ACTIVE INGREDIENTS: CLOTRIMAZOLE 10 mg/1 g
INACTIVE INGREDIENTS: SODIUM SULFITE; STEARETH-20; STEARIC ACID; WATER; PROPYLENE GLYCOL; CETOSTEARYL ALCOHOL; ETHYLPARABEN; GLYCERIN; LIGHT MINERAL OIL

Family Care Clotrimazole Cream 1% 1 oz 505

Active ingredient Purpose

Clotrimazole 1%.............................................................................Antifungal

Uses

- cures most athlete's foot, jock itch, and ringworm
- relieves itching, burning, cracking, scaling and discomfort which accompany these conditions

Warnings

For external use only

Do not use on children under 2 years of age unless directed by a doctor

When using this product avoid contact with the eyes

Stop use and ask a doctor if

- irritation occurs
- there is no improvement within 4 weeks (for athlete's foot and ringworm) or 2 weeks (for jock itch)

Keep out of reach of children. If swallowed, get medical help or contact a Poison Control Center immediately

Directions

- wash affected area and dry thoroughly
- apply a thin layer over affected area twice daily (morning and night)
- supervise children in the use of this product
- for athlete's foot: pay special attention to spaces between the toes; wear well-fitting, ventilated shoes and change shoes and socks at least once daily
- for athlete's foot and ringworm, use daily for 4 weeks; for jock itch, use daily for 2 weeks
- if condition persists longer, ask a doctor
- this product is not effective on the scalp or nails

Other information

- store between 20° to 25°C (68° to 77°F)
- Lot No. & Exp. Date: see box or see crimp of tube

Inactive ingredients

cetostearly alcohol, ethylparaben, glycerin, light mineral oil, propylene glycol, purified water, sodium sulfite, steareth-20, stearic acid

DOSAGE AND ADMINISTRATION

Distributed by:

United Exchange Corp.

5836 Corporate Ave.

Cypress, CA 90630 USA

Made in China